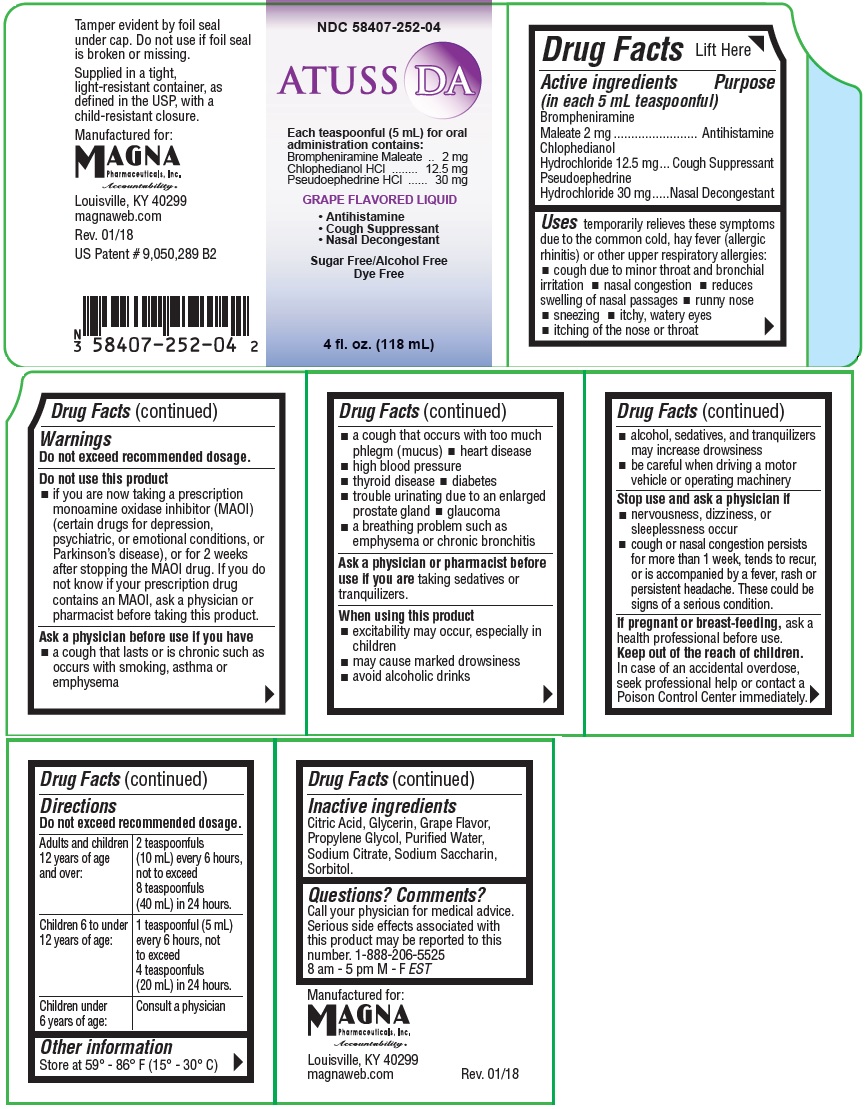 DRUG LABEL: ATUSS DA
NDC: 58407-252 | Form: LIQUID
Manufacturer: Magna Pharmceuticals, Inc.
Category: otc | Type: HUMAN OTC DRUG LABEL
Date: 20211102

ACTIVE INGREDIENTS: BROMPHENIRAMINE MALEATE 2 mg/5 mL; CHLOPHEDIANOL HYDROCHLORIDE 12.5 mg/5 mL; PSEUDOEPHEDRINE HYDROCHLORIDE 30 mg/5 mL
INACTIVE INGREDIENTS: GLYCERIN; ANHYDROUS CITRIC ACID; SORBITOL; PROPYLENE GLYCOL; WATER; SODIUM CITRATE; SACCHARIN SODIUM

ATUSS DA

Active ingredients

(in each 5mL teaspoonful)

Brompheniramine Maleate 2 mg

Chlophedianol Hydrochloride 12.5 mg

Pseudoephedrine Hydrochloride 30 mg

Purpose

Antihistamine

Cough Suppressant

Nasal Decongestant

INDICATIONS AND USAGE

Uses temporarily relieves these symptoms due to the common cold, hay fever (allergic rhinitis) or other upper respiratory allergies:

- cough due to minor throat and bronchial irritation
- nasal congestion
- reduces swelling of nasal passages
- runny nose
- sneezing
- itchy, watery eyes
- itching of the nose or throat

Warnings

Do not exceed recommended dosage.

Do not use this product

- if you are now taking a prescription monoamine oxidase inhibitor (MAOI) (certain drugs for depression, psychiatric, or emotional conditions, or Parkinson's disease), or for 2 weeks after stopping the MAOI drug. If you do not know if your prescription drug contains an MAOI, ask a physician or pharmacist before taking this product.

Ask a physician before use if you have

- a cough that lasts or is chronic such as occurs with smoking, asthma or emphysema
- a cough that occurs with too much phlegm (mucus)
- heart disease
- high blood pressure
- thyroid disease
- diabetes
- trouble urinating due to an enlarged prostate gland
- glaucoma
- a breathing problem such as emphysema or chronic bronchitis

ASK DOCTOR/PHARMACIST

Ask a physician or pharmacist before use if you are taking sedatives or tranquilizers.

When using this product

- excitability may occur, especially in children
- may cause marked drowsiness
- avoid alcoholic drinks
- alcohol, sedatives, and tranquilizers may increase drowsiness
- be careful when driving a motor vehicle or operating machinery

Stop use and ask a physician if

- nervousness, dizziness, or sleeplessness occur
- cough or nasal congestion persists for more than 1 week, tends to recur, or is accompanied by a fever, rash or persistent headache. These could be signs of a serious condition.

PREGNANCY OR BREAST FEEDING

If pregnant or breast-feeding, ask a health professional befor use.

Keep out of the reach of children.

In case of an accidental overdose, seek professional help or contact a Poison Control Center immediately.

Directions

Do not exceed recommended dosage.

Adults and children 12 years of age and over: | 2 teaspoonfuls (10 mL) every 6 hours, not to exceed 8 teapoonfuls (40 mL) in; 24 hours.
Children 6 to under 12 years of age: | 1 teaspoonful (5 mL) every 6 hours, not to exceed 4 teaspoonfuls (20 mL) in; 24 hours.
Children under 6 years of age: | Consult a physician

Other information

Store at 59° - 86°F (15° - 30°C)

Inactive ingredients

Citric Acid, Glycerin, Grape Flavor, Propylene Glycol, Purified Water, Sodium Citrate, Sodium Saccharin, Sorbitol.

Questions? Comments?

Call your physician for medical advice. Serious side effects associated with this product may be reported to this number. 1-888-206-5525, 8 am - 5 pm, M-F EST

Manufactured for:

MAGNA

Phamaceuticals, Inc.

Accountability.

Louisvill, KY 40299

magnaweb.com

Rev. 01/18